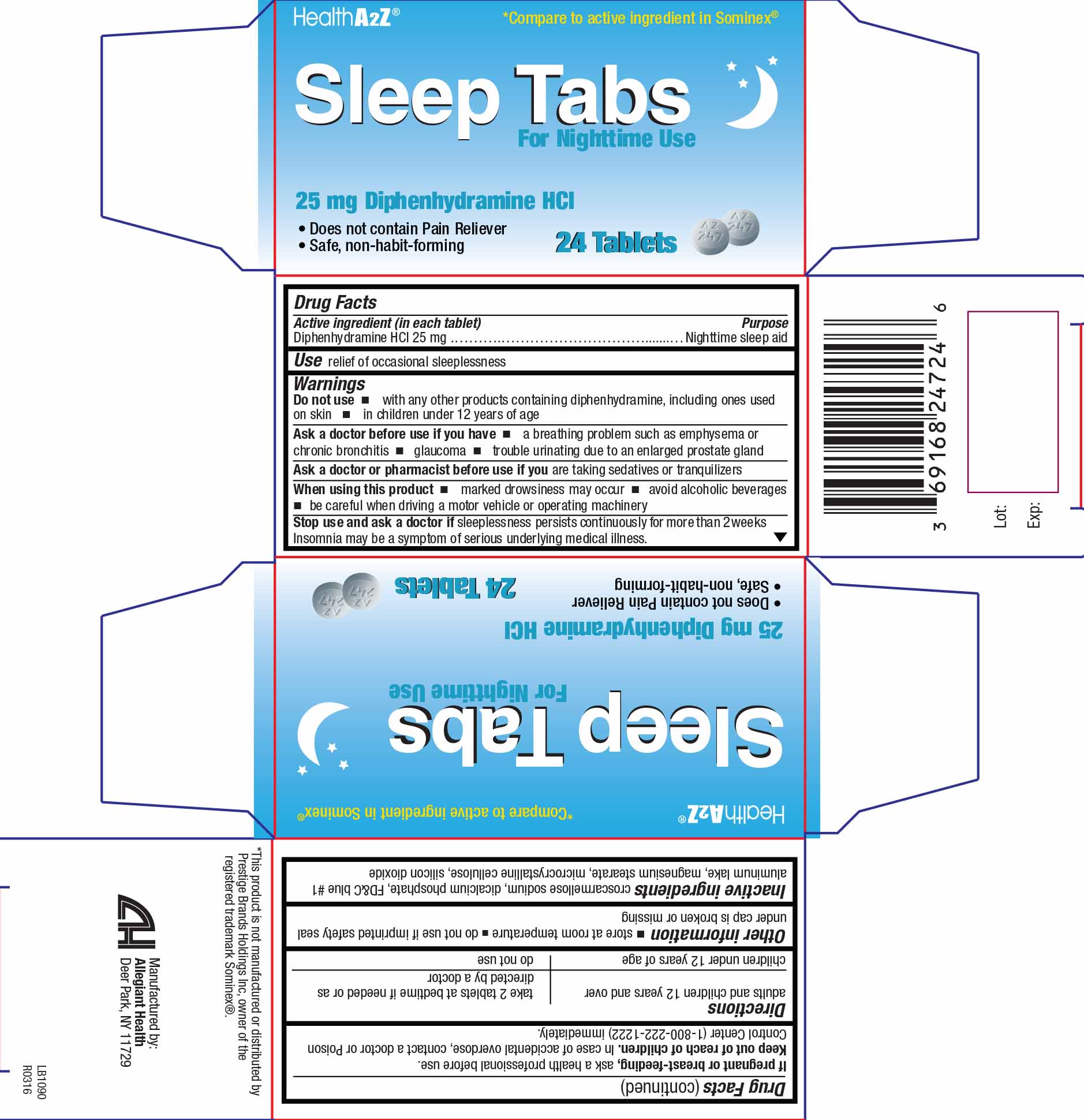 DRUG LABEL: Sleep Tabs
NDC: 69168-247 | Form: TABLET
Manufacturer: Allegiant Health
Category: otc | Type: HUMAN OTC DRUG LABEL
Date: 20181226

ACTIVE INGREDIENTS: DIPHENHYDRAMINE HYDROCHLORIDE 25 mg/1 1
INACTIVE INGREDIENTS: SILICON DIOXIDE; CROSCARMELLOSE SODIUM; FD&C BLUE NO. 1; HYPROMELLOSES; LACTOSE, UNSPECIFIED FORM; MAGNESIUM STEARATE; CELLULOSE, MICROCRYSTALLINE; POLYETHYLENE GLYCOL, UNSPECIFIED; TITANIUM DIOXIDE

Drug Facts

Active ingredient

Diphenhydramine HCl 25 mg

Purpose

Nighttime sleep aid

Uses

relief of occasional sleeplessness

Warnings

Do not use

- with any other products containing diphenhydramine, including one used on skin
- in children under 12 years of age

Ask a doctor before use if you have

- a breathing problem such as emphysema or chronic bronchitis
- glaucoma
- trouble urinating due to an enlarged prostate gland

Ask a doctor or pharmacist before use if you

are taking sedatives or tranquilizers

When using this product

- marked drowsiness may occur
- avoid alcoholic beverages
- do not drive a motor vehicle or operate machinery

Stop use and ask a doctor if

sleeplessness persists continuously for more than 2 weeks. Insomnia may be a symptom of serious underlying medical illness.

If pregnant or breast-feeding, ask a health professional before use.

Keep out of reach of children

In case of accidental overdose, contact a doctor or Poison Control Center (1-800-222-1222) immediately.

Directions

Adults and children 12 years and over | take 2 tablets at bedtime if needed or as directed by a doctor
Children under 12 years of age | do not use

Inactive Ingredients

croscarmellose sodium, dicalcium phosphate, FD&C blue #1 aluminum lake, magnesium stearate, microcrystalline cellulose, silicon dioxide

Package/Label Principal Display Panel

Diphenhydramine HCl 25mg